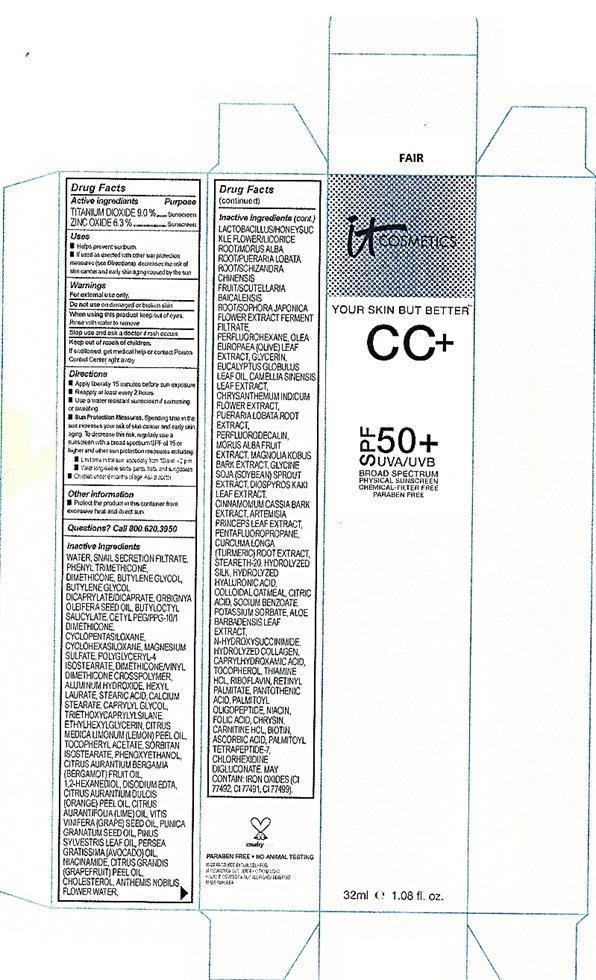 DRUG LABEL: YOUR SKIN BUT BETTER

NDC: 69259-1101 | Form: CREAM
Manufacturer: IT COSMETICS, LLC
Category: otc | Type: HUMAN OTC DRUG LABEL
Date: 20251222

ACTIVE INGREDIENTS: TITANIUM DIOXIDE 9 g/100 mL; ZINC OXIDE 6.3 g/100 mL
INACTIVE INGREDIENTS: WATER; BUTYLENE GLYCOL; PHENYL TRIMETHICONE; BUTYLENE GLYCOL DICAPRYLATE/DICAPRATE; BUTYLOCTYL SALICYLATE; MAGNESIUM SULFATE ANHYDROUS; POLYGLYCERYL-4 ISOSTEARATE; ALUMINUM HYDROXIDE; HEXYL LAURATE; STEARIC ACID; CALCIUM STEARATE; CAPRYLYL GLYCOL; TRIETHOXYCAPRYLYLSILANE; ETHYLHEXYLGLYCERIN; SORBITAN ISOSTEARATE; PHENOXYETHANOL; 1,2-HEXANEDIOL; MAGNESIUM DISODIUM EDTA; LIME OIL; GRAPE SEED OIL; PUNICA GRANATUM SEED OIL; AVOCADO OIL; NIACINAMIDE; WHITE PINE OIL; GRAPEFRUIT OIL; CHOLESTEROL; GLYCERIN; EUCALYPTUS OIL; GREEN TEA LEAF; SOYBEAN OIL; PENTAFLUOROPROPANE; TURMERIC; STEARETH-20; SILK, BASE HYDROLYZED (1000 MW); HYALURONIC ACID; OATMEAL; CITRIC ACID MONOHYDRATE; SODIUM BENZOATE; POTASSIUM SORBATE; ALOE VERA LEAF; N-HYDROXYSUCCINIMIDE; HYDROLYSED MARINE COLLAGEN (ENZYMATIC; 2000 MW); CAPRYLHYDROXAMIC ACID; TOCOPHEROL; THIAMINE HYDROCHLORIDE; RIBOFLAVIN; RETINOL; PANTOTHENIC ACID; PALMITOYL OLIGOPEPTIDE; NIACIN; FOLIC ACID; CHRYSIN; CARNITINE HYDROCHLORIDE, (+)-; BIOTIN; ASCORBIC ACID; PALMITOYL TETRAPEPTIDE-7; CHLORHEXIDINE; FERRIC OXIDE RED

Active ingredients

Titanium dioxide 9.0%

Zinc oxide 6.3%%

Purpose

Sunscreen

Uses

- helps prevent sunburn
- if used as directed with other sun protection measures (see Directions), decreases the risk of skin cancer and early skin aging caused by the sun

Warnings

For external use only

Do not use

on damaged or broken skin

When using this product

keep out of eyes. Rinse with water to remove.

Stop use and ask a doctor if

rash occurs

Keep out of reach of children.

If swallowed, get medical help or contact a Poison Control Center right away.

Directions

For sunscreen use:
● apply liberally 15 minutes before sun exposure
● reapply at least every 2 hours
● use a water resistant sunscreen if swimming or sweating
● Sun Protection Measures. Spending time in the sun increases your risk of skin cancer and early skin aging. To decrease this risk, regularly use a sunscreen with a Broad Spectrum SPF value of 15 or higher and other sun protection measures including:
● limit time in the sun, especially from 10 a.m. – 2 p.m.
● wear long-sleeved shirts, pants, hats, and sunglasses
● children under 6 months of age: Ask a doctor

Other information

protect the product in this container from excessive heat and direct sun

Inactive ingredients

Water, Butylene Glycol, Phenyl Trimethicone, Dimethicone, Snail Secretion Filtrate, Butylene Glycol Dicaprylate/Dicaprate, Orbignya Oleifera Seed Oil, Butyloctyl Salicylate, Cetyl PEG/PPG-10/1 Dimethicone, Cyclopentasiloxane, Cyclohexasiloxane, Magnesium Sulfate, Polyglyceryl-4 Isostearate, Dimethicone/Vinyl Dimethicone Crosspolymer, Aluminum Hydroxide, Hexyl Laurate, Stearic Acid, Calcium Stearate, Caprylyl Glycol, Triethoxycaprylylsilane, Ethylhexylglycerin, Phenoxyethanol, Citrus Medica Limonum (Lemon) Peel Oil, Tocopheryl Acetate, Sorbitan Isostearate, Citrus Aurantium Bergamia (Bergamot) Fruit Oil, 1,2-Hexanediol, Water, Disodium EDTA, Citrus aurantium dulcis (orange) peel essential oil, Citrus Aurantifolia (Lime) Essential Oil, Vitis Vinifera (Grape) Seed Oil, Punica Granatum Seed Oil, Pinus Sylvestris Leaf Essential Oil, Persea Gratissima (Avocado) Oil, Niacinamide, Citrus Grandis (Grapefruit) Peel Oil, Anthemis Nobilis Flower Water, Lactobacillus/Honeysuckle Flower/Licorice Root/Morus Alba Root/Pueraria Lobata Root/Schizandra Chinensis Fruit/Scutellaria Baicalensis Root/Sophora Japonica Flower Extract Ferment Filtrate, Perfluorohexane, Olea Europaea (Olive) Leaf Extract, Glycerin, Eucalyptus Essential Oil, Cholesterol, Camellia Sinensis Leaf Extract, Chrysanthemum Indicum flower Extract, Pueraria Lobata Root Extract, Perfluorodecalin, Morus Alba Fruit Extract, Magnolia Kobus Bark Extract, Glycine Soja (Soybean) Sprout Extract, Diospyros Kaki Leaf Extract, Cinnamomum Cassia Bark Extract, Artemisia Princeps Leaf Extract, Pentafluoropropane, Curcuma Longa (Turmeric) Root Extract, Steareth-20, Hydrolyzed Hyaluronic Acid, Colloidal Oatmeal, Hydrolyzed Silk, Citric Acid, Sodium Benzoate, Potassium sorbate, Aloe Barbadensis Leaf Extract, N-Hydroxysuccinimide, Hydrolyzed Collagen, Caprylhydroxamic Acid, Tocopherol, Thiamine HCl, Riboflavin, Retinyl Palmitate, Pantothenic Acid, Palmitoyl Oligopeptide, Niacin, Folic Acid, Chrysin, Carnitine HCl, Biotin, Ascorbic Acid, Palmitoyl Tetrapeptide-7, Chlorhexidine Digluconate, Iron Oxides (CI 77492, CI 77491, CI 77499).

Questions or comments?

Call 800-620-3950